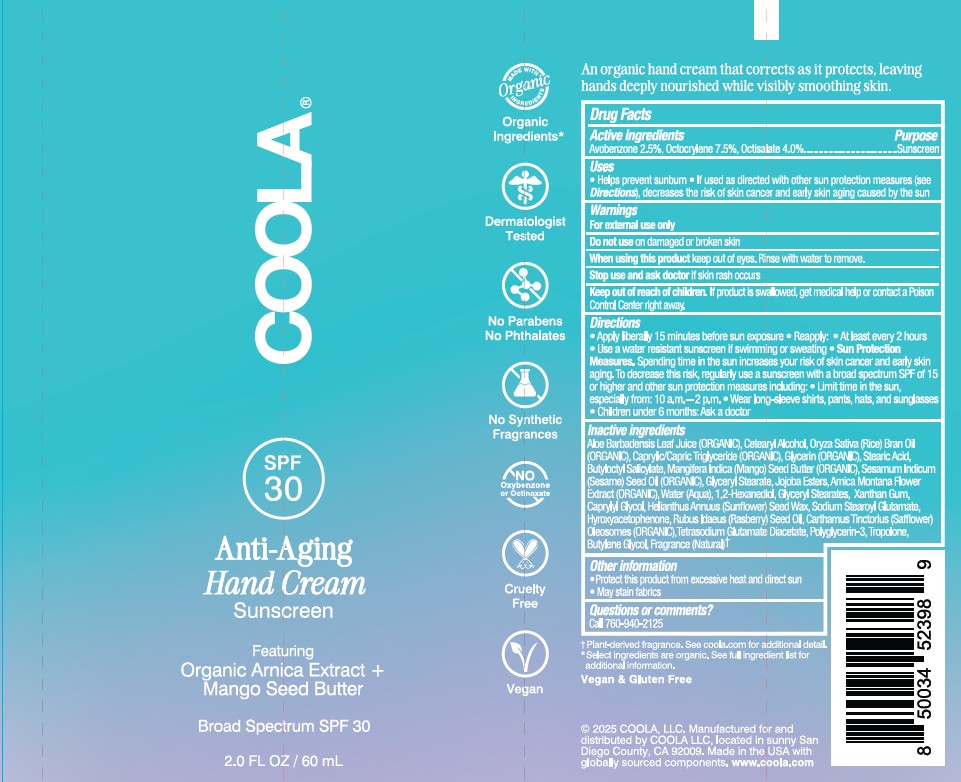 DRUG LABEL: Coola Anti-Aging Hand Cream Sunscreen
NDC: 79753-105 | Form: CREAM
Manufacturer: COOLA LLC
Category: otc | Type: HUMAN OTC DRUG LABEL
Date: 20250812

ACTIVE INGREDIENTS: AVOBENZONE 2.5 g/100 mL; OCTISALATE 4 g/100 mL; OCTOCRYLENE 7.5 g/100 mL
INACTIVE INGREDIENTS: TROPOLONE; CETEARYL ALCOHOL; STEARIC ACID; ALOE BARBADENSIS LEAF JUICE; ORYZA SATIVA (RICE) BRAN; GLYCERIN; HYDROXYACETOPHENONE; RUBUS IDAEUS (RASPBERRY) SEED OIL; HYDROLYZED JOJOBA ESTERS; CAPRYLYL GLYCOL; ARNICA MONTANA FLOWER; BUTYLENE GLYCOL; SESAMUM INDICUM (SESAME) SEED OIL; XANTHAN GUM; BUTYLOCTYL SALICYLATE; CAPRYLIC/CAPRIC TRIGLYCERIDE; MANGIFERA INDICA (MANGO) SEED BUTTER; GLYCERYL STEARATE; 1,2-HEXANEDIOL; TETRASODIUM GLUTAMATE DIACETATE; POLYGLYCERIN-3; SODIUM STEAROYL GLUTAMATE; HELIANTHUS ANNUUS (SUNFLOWER) SEED WAX; WATER; CARTHAMUS TINCTORIUS (SAFFLOWER) OLEOSOMES

Coola Anti-Aging Hand Cream Sunscreen

Active ingredients

Avobenzone, Octocrylene, Octisalate

Purpose

Avobenzone 2.5%, Octocrylene 7.5%, Octisalate 4.0%..................Sunscreen

Uses

- Helps prevent sunburn
- If used as directed with other sun protection measures (see Directions), decreases the risk of skin cancer and early skin aging caused by the sun

Warnings

For external use only

Do not use on damaged or broken skin

When using this product keep out of eyes. Rinse with water to remove.

Stop use and ask doctor if skin rash occurs.

Keep out of reach of children. If product is swallowed, get medical help or contact a Poison Control Center right away.

Directions

- Apply liberally 15 minutes before sun exposure
- Reapply:
- At least every 2 hours
- Use a water resistant sunscreen if swimming or sweating
- Sun Protection Measures. Spending time in the sun increases your risk of skin cancer and early skin aging. To decrease this risk, regularly use a sunscreen with a broad spectrum SPF of 15 or higher and other sun protection measures including:
- Limit time in the sun, especially from: 10 a.m.-2 p.m.
- Wear long-sleeve shirts, pants, hats, and sunglasses
- Children under 6 months: Ask a doctor

Inactive ingredients

Aloe Barbadensis Leaf Juice (ORGANIC); Cetearyl Alcohol, Oryza Sativa (Rice) Bran Oil (ORGANIC); Caprylic/Capric Triglycderide (ORGANIC); Glycerin (ORGANIC); Stearic Acid, Butyloctyl Salicylate, Mangifera Indica (Mango) Seed Butter (ORGANIC); Sesamum Indicum (Sesame) Seed Oil (ORGANIC); Glyceryl Stearate; Jojoba Esters; Arnica Montana FLower Extract (ORGANIC); Water (Aqua); 1,2-Hexanediol; Glyceryl Stearates; Xanthan Gum; Caprylyl Glycol; Helianthus Annuus (Sunflower) Seed Wax; Sodium Stearoyl Glutamate; Hyroxyacetophenone; Rubus Idaeus (Raspberry) Seed Oil; Carthamus Tinctorius (Safflower) Oleosomes (ORGANIC); Tetrasodium Glutamate Diacetate; Polyglycerin-3; Tropolone; Butylene Glycol; Fragrance (Natural)

Other information

- Protect this product from excessive heat and direct sun
- May stain fabrics

Questions or comments?

Call 760-940-2125

PACKAGE LABEL

COOLA

SPF 30

Anti-Aging

Hand Cream

Sunscreen

Featuring

Organic Arnica Extract +

Mango Seed Butter

Broad Spectrum SPF 30

2.0 FL OZ / 60 mL